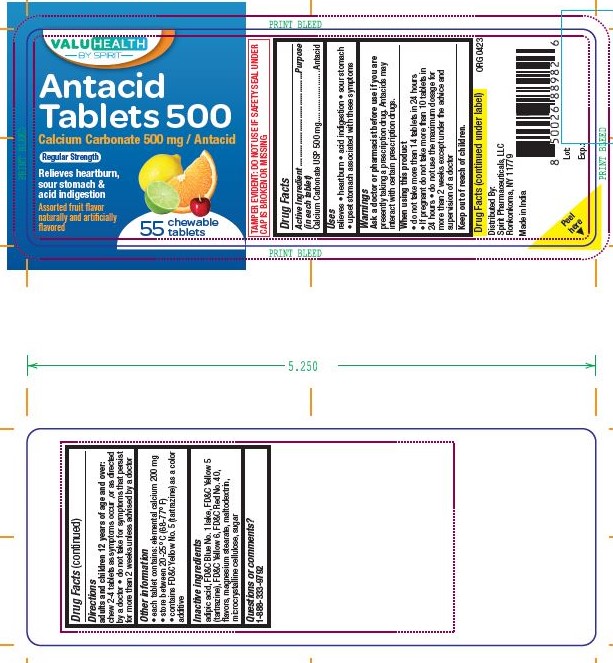 DRUG LABEL: Calcium Carbonate 500mg
NDC: 68210-5033 | Form: TABLET, CHEWABLE
Manufacturer: Spirit Pharmaceuticals LLC
Category: otc | Type: HUMAN OTC DRUG LABEL
Date: 20241211

ACTIVE INGREDIENTS: CALCIUM CARBONATE 500 mg/1 1
INACTIVE INGREDIENTS: ADIPIC ACID; FD&C BLUE NO. 1; FD&C YELLOW NO. 5; FD&C YELLOW NO. 6; FD&C RED NO. 40; MAGNESIUM STEARATE; MALTODEXTRIN; MICROCRYSTALLINE CELLULOSE; SUCROSE

VALUHEALTH BY SPIRIT

When using this product

- do not take more than 14 tablets in 24 hours
- if pregnant do not take more than 10 tablets in 24 hours
- do not use the maximum dosage for more than 2 weeks except under the advice and supervision of a doctor

Other information

- each tablet contains: elemental calcium 200 mg
- store between 20-25° C (68-77°)
- contains FD&C Yello No. 5 (tartrazine) as a color additive